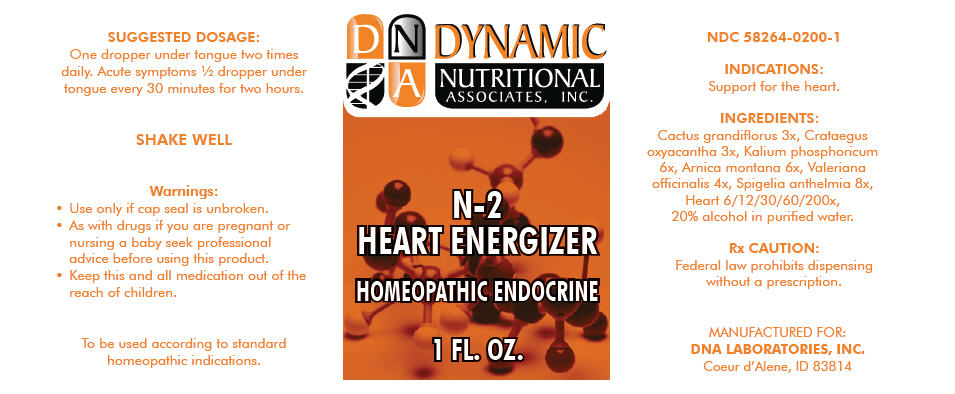 DRUG LABEL: N-2
NDC: 58264-0200 | Form: SOLUTION
Manufacturer: DNA Labs, Inc.
Category: homeopathic | Type: HUMAN OTC DRUG LABEL
Date: 20250109

ACTIVE INGREDIENTS: SELENICEREUS GRANDIFLORUS WHOLE 3 [hp_X]/1 mL; CRATAEGUS LAEVIGATA WHOLE 3 [hp_X]/1 mL; DIBASIC POTASSIUM PHOSPHATE 6 [hp_X]/1 mL; ARNICA MONTANA 6 [hp_X]/1 mL; VALERIANA OFFICINALIS WHOLE 4 [hp_X]/1 mL; SPIGELIA ANTHELMIA 8 [hp_X]/1 mL; BEEF HEART 200 [hp_X]/1 mL
INACTIVE INGREDIENTS: ALCOHOL; WATER

N-2

NDC 58264-0200-1

INDICATIONS AND USAGE

INDICATIONS

Support for the heart.

ACTIVE INGREDIENT

INGREDIENTS

Cactus grandiflorus 3x, Crataegus oxyacantha 3x, Kalium phosphoricum 6x, Arnica montana 6x, Valeriana officinalis 4x, Spigelia anthelmia 8x, Heart 6/12/30/60/200x, 20% alcohol in purified water.

Rx CAUTION

Federal law prohibits dispensing without a prescription.

SUGGESTED DOSAGE

One dropper under tongue two times daily. Acute symptoms ½ dropper under tongue every 30 minutes for two hours.

STORAGE AND HANDLING

SHAKE WELL

Warnings

- Use only if cap seal is unbroken.

PREGNANCY OR BREAST FEEDING

- As with drugs if you are pregnant or nursing a baby seek professional advice before using this product.

KEEP OUT OF REACH OF CHILDREN

- Keep this and all medication out of the reach of children.

To be used according to standard homeopathic indications.

PRINCIPAL DISPLAY PANEL - 1 FL. OZ. Bottle Label

DYNAMIC
NUTRITIONAL
ASSOCIATES, INC.

N-2
HEART ENERGIZER

HOMEOPATHIC ENDOCRINE

1 FL. OZ.